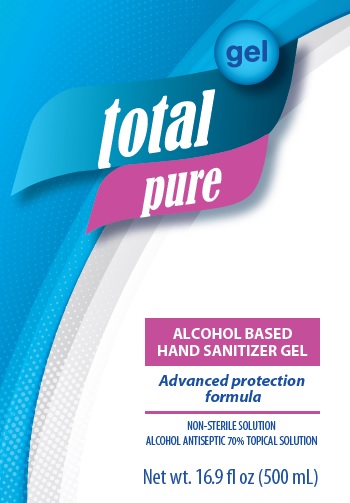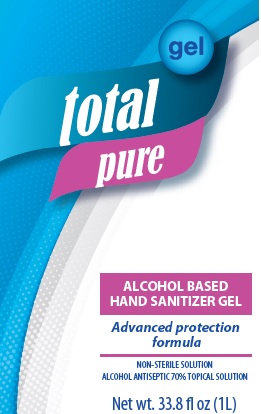 DRUG LABEL: ALCOHOL BASED HAND SANITIZER TOTAL PURE
NDC: 51384-003 | Form: GEL
Manufacturer: BOTANICALS INTERNACIONAL S.A. DE C.V.
Category: otc | Type: HUMAN OTC DRUG LABEL
Date: 20200617

ACTIVE INGREDIENTS: ALCOHOL 70 mL/100 mL
INACTIVE INGREDIENTS: CARBOMER 940 0.25 mL/100 mL; TROLAMINE 0.25 mL/100 mL; WATER 29.3 mL/100 mL; GLYCERIN 0.2 mL/100 mL

total pure ALCOHOL BASED HAND SANITIZER

ACTIVE INGREDIENT

Ethyl Alcohol 70% v/v

PURPOSE

Antimicrobial

INDICATIONS AND USAGE

- Hand Sanitizer to help reduce bacteria that potentially can cause disease.
- For use when soap and water are not available.

INACTIVE INGREDIENTS

Water, Carbomer, Triethanolamine. and Glycerine

KEEP OUT OF REACH SECTION

Keep out of reach of children. If swallowed, get medical help or contact a Poison Control Center right away.

Directions

• Place enough product in your palm to cover hands and rub hands together briskly until dry.
• Children under 6 years of age should be surpervised when using this product.

When using this product

Do not use near or in the eyes.

In case of contact, rinse eyes thoroughly with water.

Stop use

Stop use and ask a doctor if irritation or rash appears and lasts.

WARNINGS

Flammable

Keep away from heat or flame.
For external use only.

Principal Display Panel

500ML NDC: 51384-003-002